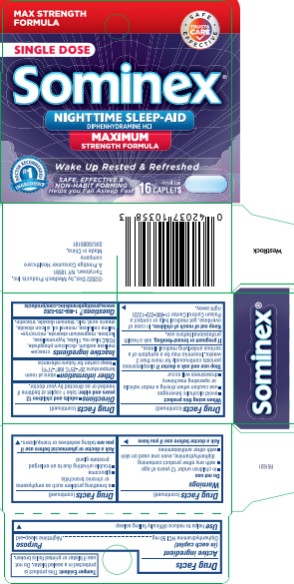 DRUG LABEL: Sominex Max
NDC: 63029-505 | Form: TABLET
Manufacturer: Medtech Products Inc.
Category: otc | Type: HUMAN OTC DRUG LABEL
Date: 20251023

ACTIVE INGREDIENTS: DIPHENHYDRAMINE HYDROCHLORIDE 50 mg/1 1
INACTIVE INGREDIENTS: CROSCARMELLOSE SODIUM; CALCIUM PHOSPHATE, DIBASIC, DIHYDRATE; FD&C BLUE NO. 1; HYPROMELLOSE, UNSPECIFIED; LACTOSE, UNSPECIFIED FORM; MAGNESIUM STEARATE; CELLULOSE, MICROCRYSTALLINE; MINERAL OIL; SILICON DIOXIDE; STEARIC ACID; TALC; TITANIUM DIOXIDE; TRIACETIN

Sominex Max

Drug Facts

Active ingredient

(in each caplet)

Diphenhydramine HCl 50 mg

Purpose

Nighttime sleep-aid

Use

Helps to reduce difficultly falling asleep

Warnings

Do not use

- in children under 12 years of age
- with any other product containing diphenhydramine, even one used on skin
- with other antihistamines

Ask a doctor before use if you have

- a breathing problem such as emphysema or chronic bronchitis
- glaucoma
- trouble urinating due to an enlarged prostate gland

Ask a doctor or pharmacist before use if you are

taking sedatives or tranquilizers

When using this product

- avoid alcoholic beverages
- be careful when driving a motor vehicle or operating machinery
- drowsiness will occur

Stop use and ask a doctor if

sleeplessness persists continuously for more than 2 weeks. Insomnia may be a symptom of serious underlying medical illness.

If pregnant or breast-feeding,

ask a health professional before use.

Keep out of reach of children.

In case of overdose, get medical help or contact a Poison Control Center (1-800-222-1222) right away.

Directions

- adults and children 12 years and older: take 1 caplet at bedtime if needed, or as directed by your doctor

Other information

- store at room temperature 20º- 25ºC (68º-77ºF)
- keep carton for future reference

Inactive ingredients

croscarmellose sodium, dicalcium phosphate, FD&C blue no. 1 lake, hypromellose, lactose, magnesium stearate, microcrystalline cellulose, mineral oil, silica, stearate acid, talc, titanium dioxide, triacetin

Questions?

1-866-255-5202

PRINCIPAL DISPLAY PANEL

MAXIMUM STRENGTH FORMULA
Sominex®
NIGHTTIME SLEEP-AID DIPHENHYDRAMINE HCl
16 TABLETS